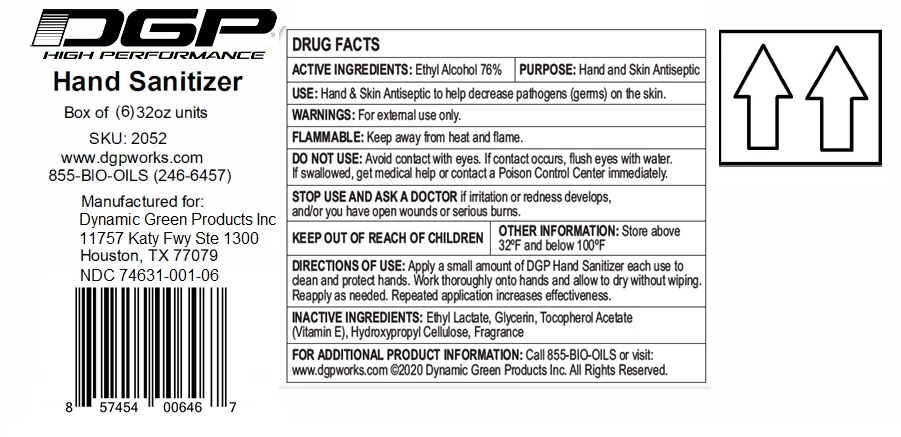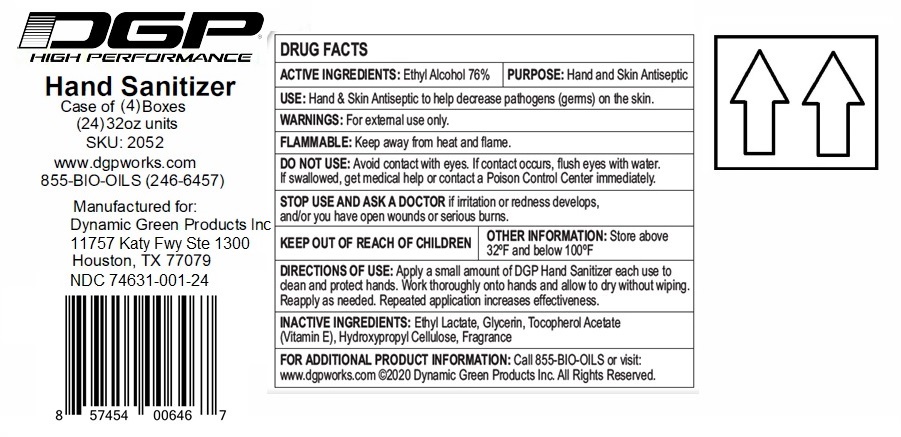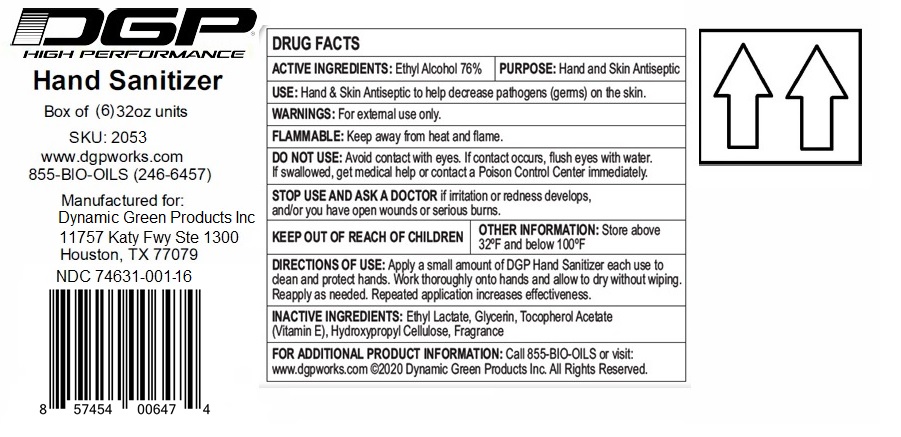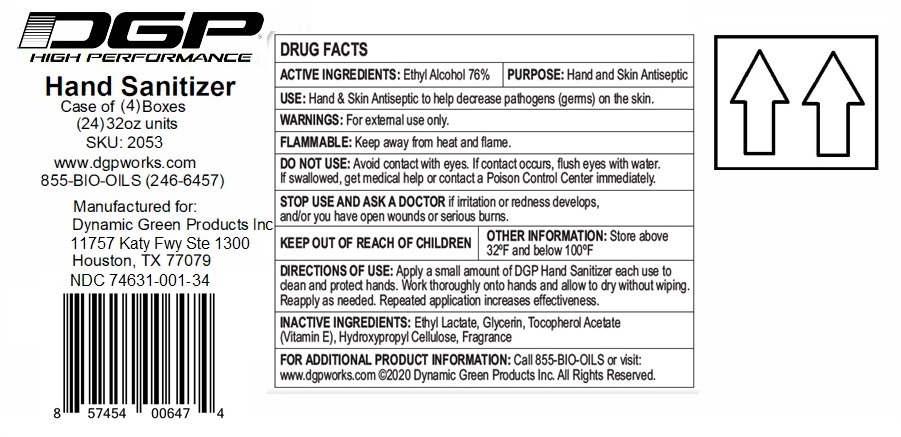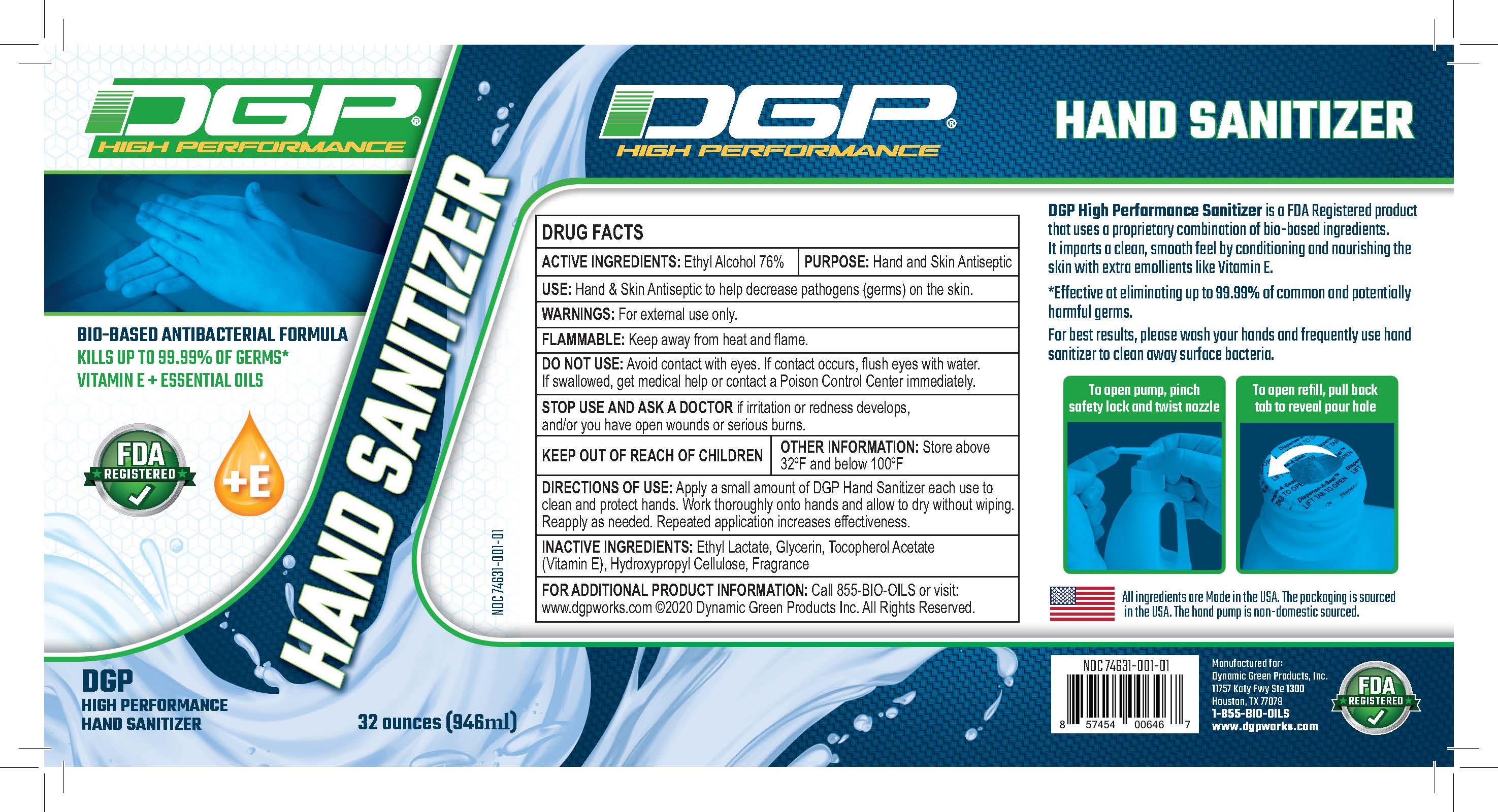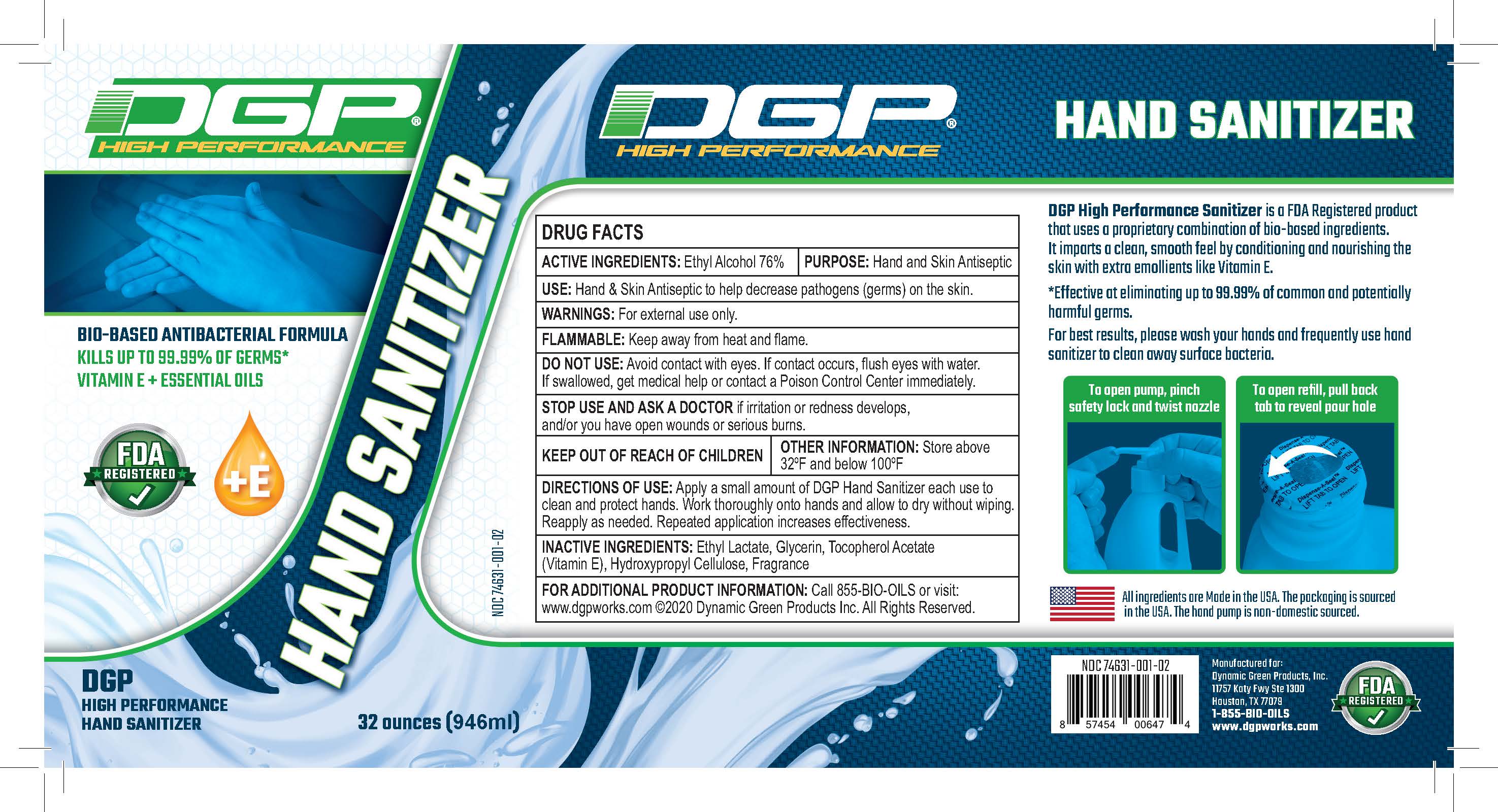 DRUG LABEL: DGP High Performance Hand Sanitizer
NDC: 74631-001 | Form: GEL
Manufacturer: Dynamic Green Products, Inc.
Category: otc | Type: HUMAN OTC DRUG LABEL
Date: 20200416

ACTIVE INGREDIENTS: ALCOHOL 76 mL/100 mL
INACTIVE INGREDIENTS: HYDROXYPROPYL CELLULOSE (110000 WAMW); GLYCERIN; .ALPHA.-TOCOPHEROL ACETATE; ETHYL LACTATE

Drug Facts

Active ingredient

Ethyl Alcohol 76%

Purpose

Hand & Skin Antiseptic

INDICATIONS AND USAGE

Hand & Skin Antiseptic to help decrease pathogens (germs) on the skin

WARNINGS

For external use only

Flammable: Keep away from heat and flame

Do not use

* Avoid contact with eyes.

* If contact occurs, flush eyes with water.

* If swallowed, get medical help or contact a Poison Control Center immediately.

As a doctor before use it you have

* Open wounds.

* Serious burns

Stop use and ask doctor it

It irritation or redness develops.

Keep out of reach of children

* Children should be supervised when using this product.

Directions

Apply a small smount of DGP Hand Sanitizer each use to clean and protect hands. Work thoroughly onto hands and allow to dry without wiping. Reapply as needed. Repeated application increases effectiveness.

Inactive ingredients

Ethyl Lactate, Glycerin, Alpha Tocopherol Acetate, Hydroxypropyl Cellulose, Peach Fragrance

Principal Display Panel

DGP(R) High Performance Hand Sanitizer

Bio-based Antibacterial Formula

Vitamin E+ Essential oils

To open pump, pinch safety lock and twist nozzle

To open refill, pull back tab to reveal pour hole

All ingredients are made in the USA

The packaging is sourced in the USA

The hand pump is non-domestic sourced.

(Manufactured for:)

Dynamic Green Products, Inc.

11757 Katy Fwy Ste 1300

Houston, TX 77079

For additional Product information: Call 855-BIO-OILS or visit: www.dgpworks.com

(C) Dynamic Green Products Inc. All Rights Reserved.

XX oz (xxx mL) NDC 74631-001-XX